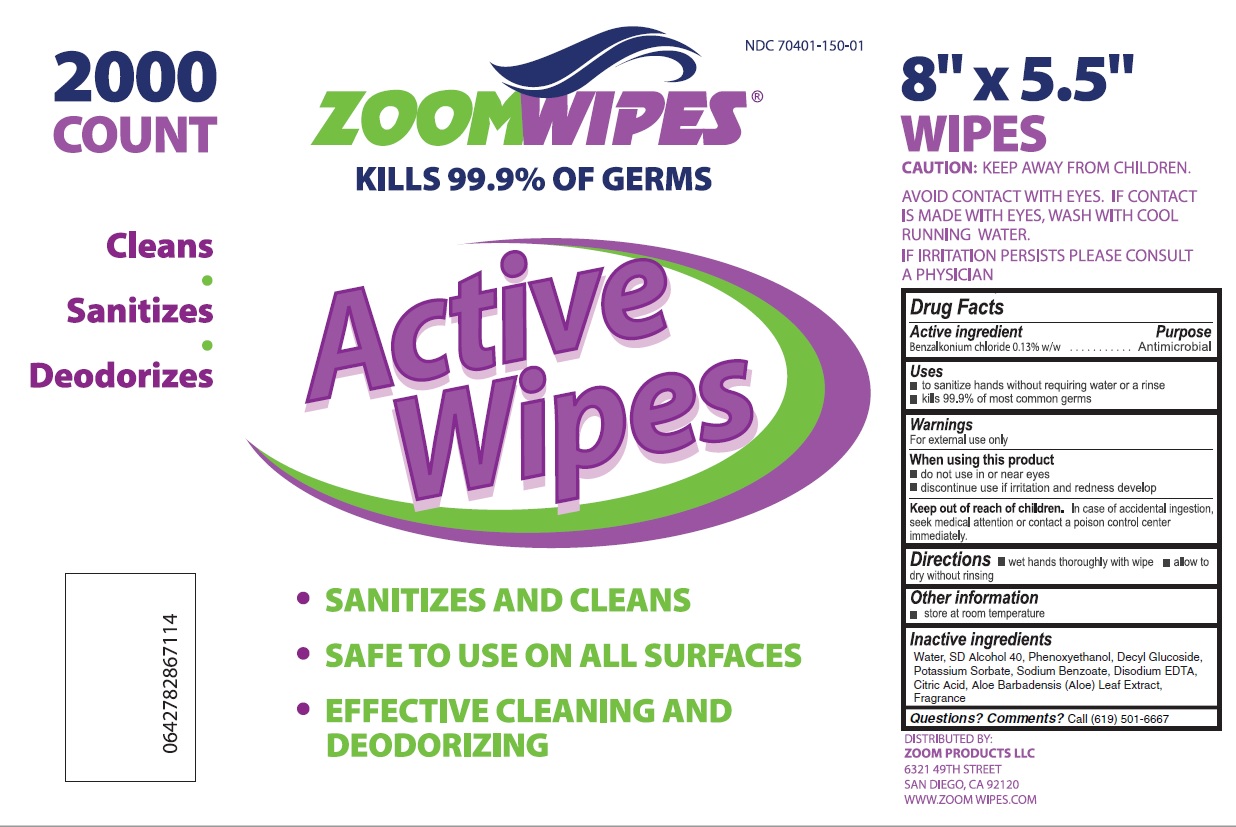 DRUG LABEL: Zoom Wipes
NDC: 70401-150 | Form: SWAB
Manufacturer: ZOOM PRODUCTS LLC
Category: otc | Type: HUMAN OTC DRUG LABEL
Date: 20241206

ACTIVE INGREDIENTS: BENZALKONIUM CHLORIDE 0.13 g/100 g
INACTIVE INGREDIENTS: WATER; PHENOXYETHANOL; DECYL GLUCOSIDE; POTASSIUM SORBATE; SODIUM BENZOATE; EDETATE DISODIUM; CITRIC ACID MONOHYDRATE; ALOE VERA LEAF

Drug Facts

Active ingredient

Benzalkonium chloride 0.13% w/w

Purpose

Antimicrobial

Uses

- to sanitize hands without requiring water or a rinse
- kills 99.9% of most common germs

Warnings

For external use only

When using this product

- do not use in or near eyes
- discontinue use if irritation and redness develop

Keep out of reach of children

In case of accidental ingestion, seek medical attention or contact a poison control center immediately.

Directions

- wet hands thoroughly with wipe
- allow to dry without rinsing

Other information

- store at room temperature

Inactive ingredients

Water, SD Alcohol 40, Phenoxyethanol, Decyl Glucoside, Potassium Sorbate, Sodium Benzoate, Disodium EDTA, Citric Acid, Aloe Barbadensis (Aloe) Leaf Extract, Fragrance

Questions? Comments?

Call (619) 501-6667

Principal Display Panel

NDC 70401-150-01

2000 count

ZOOMWIPES

KILLS 99.9% OF GERMS

Active Wipes

Cleans

Sanitizes

Deodorizes

- SANITIZES AND CLEANS
- SAFE TO USE ON ALL SURFACES
- EFFECTIVE CLEANING AND DEODORIZING